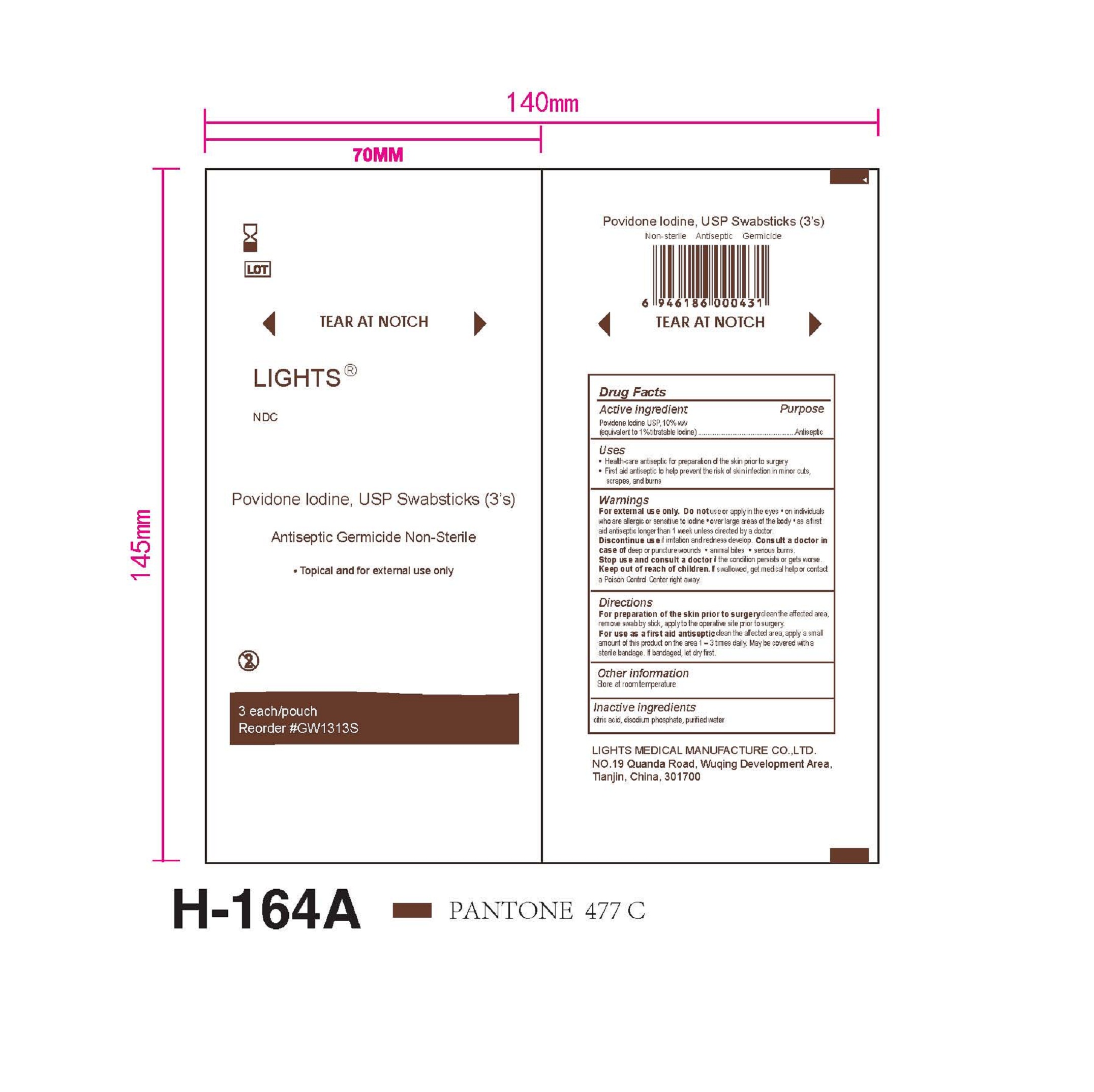 DRUG LABEL: Lights Povindone Iodine Swabstick
NDC: 61333-204 | Form: SOLUTION
Manufacturer: Lights Medical Manufacture Co., Ltd.
Category: otc | Type: HUMAN OTC DRUG LABEL
Date: 20260121

ACTIVE INGREDIENTS: POVIDONE-IODINE 1 g/100 g
INACTIVE INGREDIENTS: WATER; CITRIC ACID MONOHYDRATE; SODIUM PHOSPHATE DIBASIC DIHYDRATE

61333-204

Active Ingredient: Povidone-Iodine USP (10%)

Purpose: Antiseptic

Use:

Health care antiseptic for prepapration of skin prior to surgery.

First aid antiseptic to help prevent infection in minor cuts, scrapes and burns.

Warnings:

For external use only

Do not *use or apply to the eyes *to individuals who are allergic or sensitive to iodine, *over large area of the body, *as first aid antiseptic longer than a week unless directed by a doctor

Keep out of reach of children. If swallowed, get medical help or consult a poison control center immediately

ASK DOCTOR

Discontinue use if irritation and redness develop. Consult a doctor iin case of deep or puncture wounds, animal bites, or serious burns

Stop use and ask a doctor if infection occurs or if condition persists or increases

DOSAGE AND ADMINISTRATION

For preparation of the skin prior surgery: clean the affacted area, remove swabstick, apply to the operative site prior to surgery

For use as first aid antiseptic: clean the affacted area, apply a small anount of the product to the area 1-3 times daily. Maybe covered with a sterile bandage. If bandaged, let dry first.

Other information

- Store at room temperature

Inactive Ingredient

Citric acid, purified water, Sodium phosphate dibasic